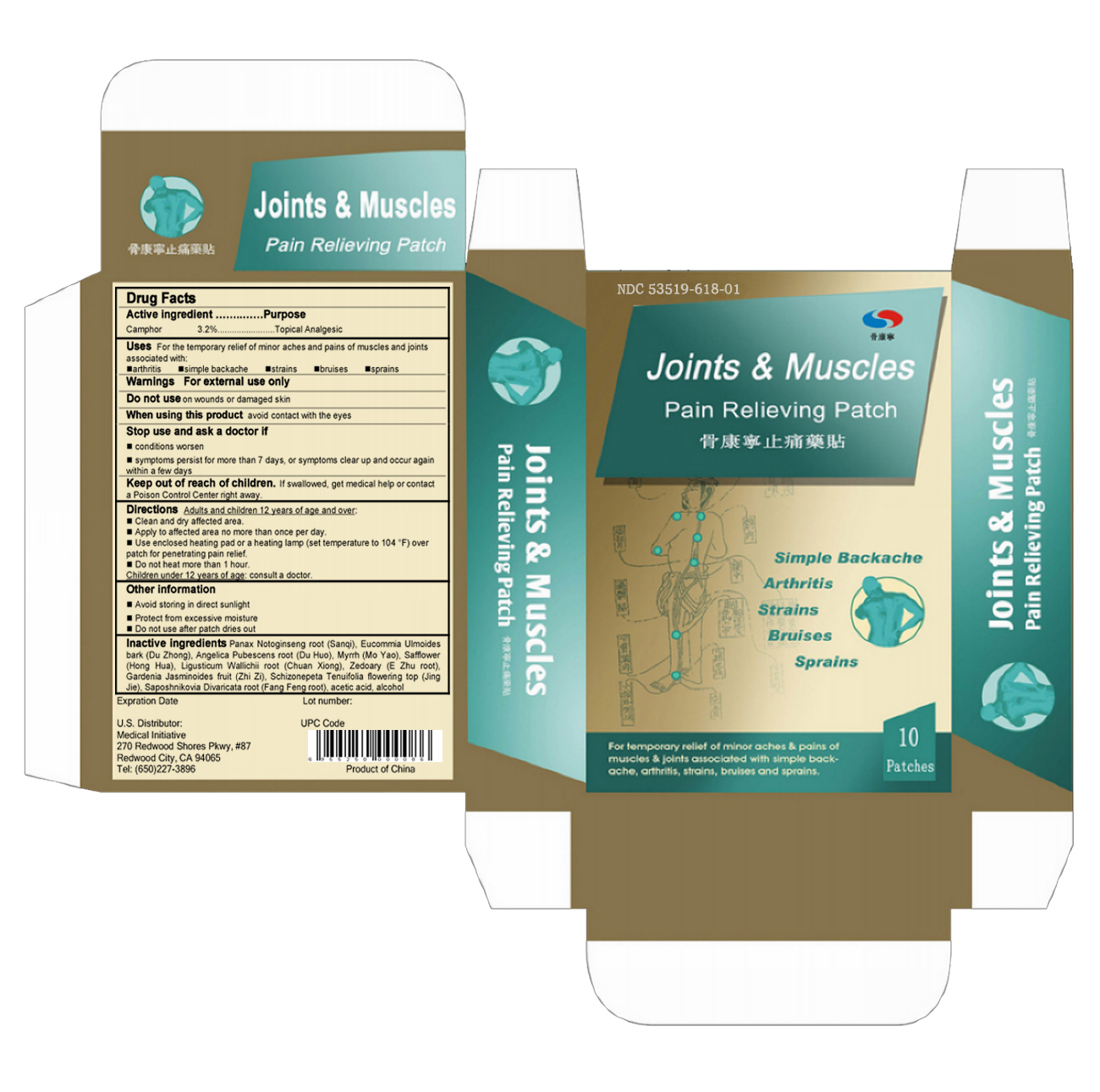 DRUG LABEL: Joints and Muscles Pain Relieving
                
NDC: 53519-618 | Form: PATCH
Manufacturer: Chongqing Yilin Science and Technology Co., Ltd.
Category: otc | Type: HUMAN OTC DRUG LABEL
Date: 20130109

ACTIVE INGREDIENTS: CAMPHOR (NATURAL) 22.5 mg/1 1
INACTIVE INGREDIENTS: PANAX NOTOGINSENG ROOT; EUCOMMIA ULMOIDES BARK; ANGELICA PUBESCENS ROOT; MYRRH; SAFFLOWER; LIGUSTICUM WALLICHII ROOT; ZEDOARY; GARDENIA JASMINOIDES FRUIT; SCHIZONEPETA TENUIFOLIA FLOWERING TOP; SAPOSHNIKOVIA DIVARICATA ROOT; ACETIC ACID; ALCOHOL

Drug Facts

Active Ingredient

Camphor (Natural) 3.2%

Purpose

Topical Analgesic

Uses

For the temporary relief of minor aches and pains of muscles and joints associated with:

- arthritis
- simple backache
- strains
- bruises
- sprains

Warnings

For external use only

Do not use

on wounds or damaged skin

When using this product

avoid contact with the eyes

Stop use and ask a doctor if

- conditions worsen
- symptoms persist for more than 7 days, or symptoms clear up and occur again within a few days

Keep out of reach of children.

If swallowed, get medical help or contact Poison Control Center right away.

Directions

Adults and children 12 years of age and over:

- Clean and dry affected area.
- Apply to affected area no more than once per day.
- Use enclosed heating pad or a heating lamp (set temperature to 104 °F) over patch for penetrating pain relief.
- Do not apply for more than 1 hour.

Children under 12 years of age: consult a doctor.

Other information

- Avoid storing in direct sunlight
- Protect from excessive moisture
- Do not use after patch dries out

Inactive ingredients

Panax Notoginseng root, Eucommia Ulmoides bark, Angelica Pubescens root, Myrrh, Safflower, Ligusticum Wallichii root, Zedoary, Gardenia Jasminoides fruit, Schizonepeta Tenuifolia flowering top, Saposhnikovia Divaricata root, acetic acid, alcohol

Carton Label Image